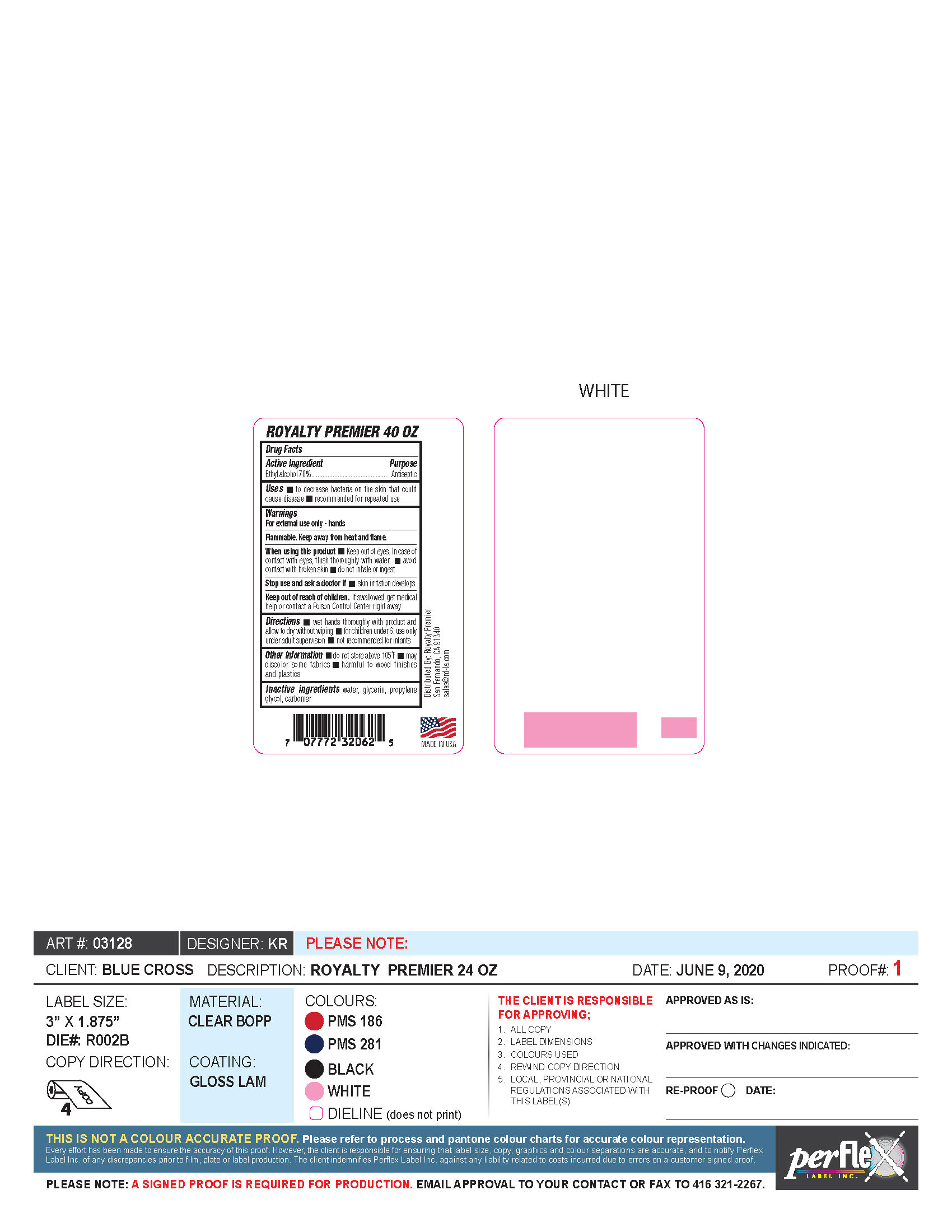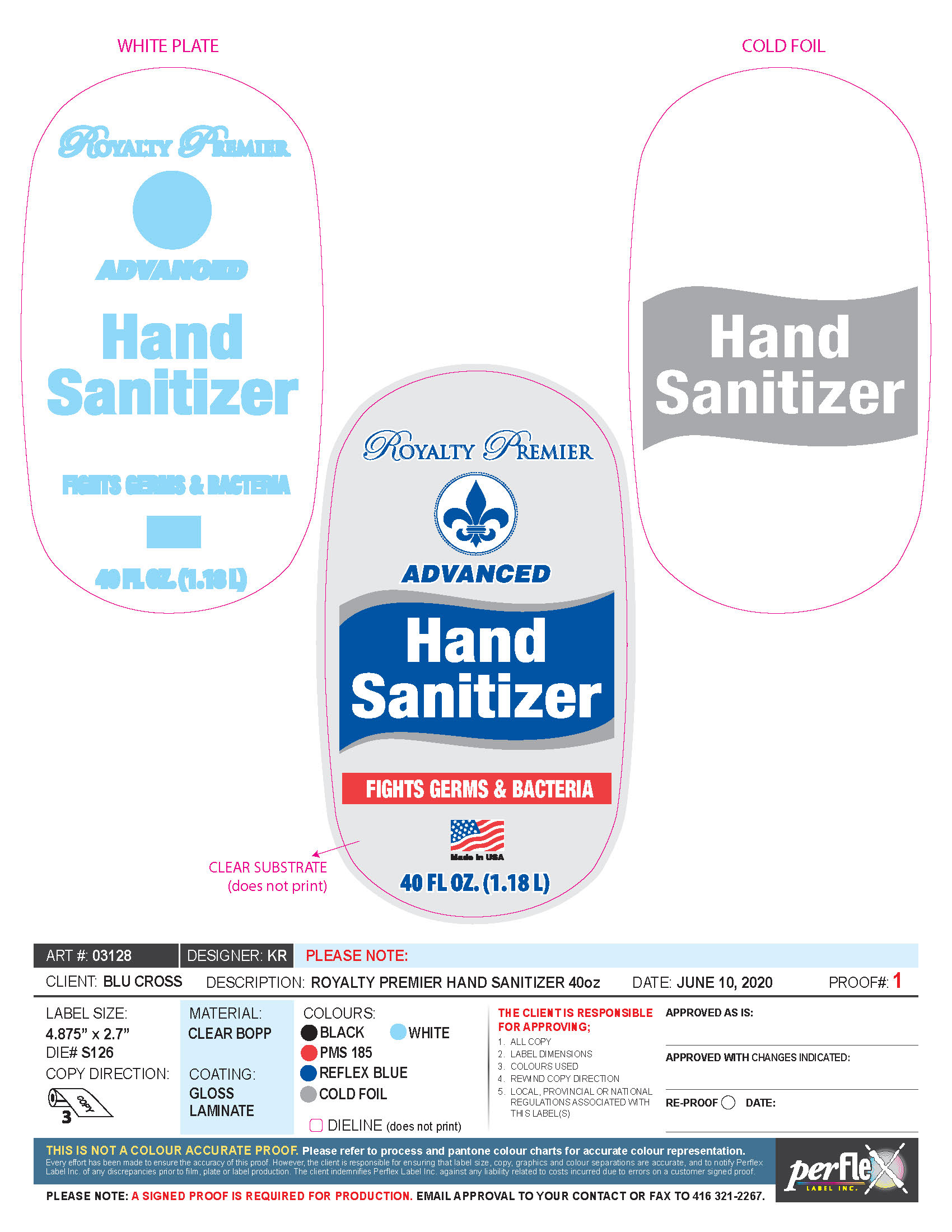 DRUG LABEL: Advanced Hand Sanitizer
NDC: 79327-001 | Form: GEL
Manufacturer: Purchasing 411, Inc.
Category: otc | Type: HUMAN OTC DRUG LABEL
Date: 20200718

ACTIVE INGREDIENTS: ALCOHOL 70 mL/100 L
INACTIVE INGREDIENTS: PROPYLENE GLYCOL; GLYCERIN; WATER; CARBOMER HOMOPOLYMER, UNSPECIFIED TYPE

Advanced Hand Sanitizer

Active Ingredient(s)

Ethyl Alcohol 70% v/v. Purpose: Antiseptic

Use

- To decrease bacteria on the skin that could cause disease.
- recommended for repeated use

Keep out of reach of children. If swallowed, get medical help or contact a Poison Control Center right away.

Stop use and ask a doctor if

- Skin irritation develops

Warnings

For external use only. Flammable. Keep away from heat or flame

When using this product

- Keep out of eyes. In case of contact with eyes, flush thoroughly with water.
- Avoid contact with broken skin
- Do not inhale or ingest

Directions

- Wet hands thoroughly with product and allow to dry without wiping
- For children under 6, use only under adult supervision
- not recommend for infants

Other information

- do not store above 105ºF
- may discolor some fabrics
- harmful to wood finishes and plasics

Inactive ingredients water, glycerin, propylene glycol,carbomer

PACKAGE LABEL

Royalty Premier

Advanced

Hand Sanitizer

Fights Germs and Bacteria

40 FL OZ (1.18 L)